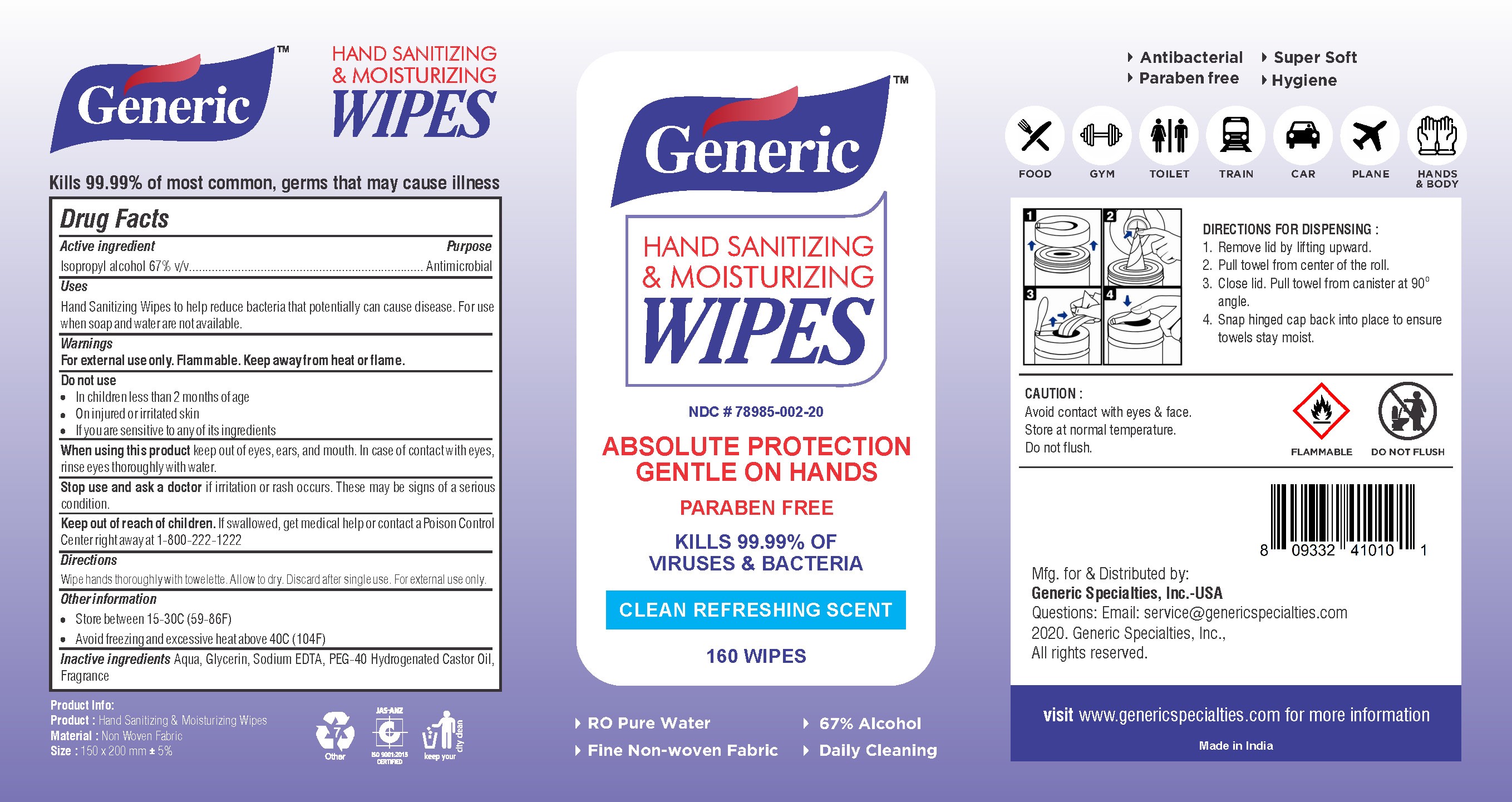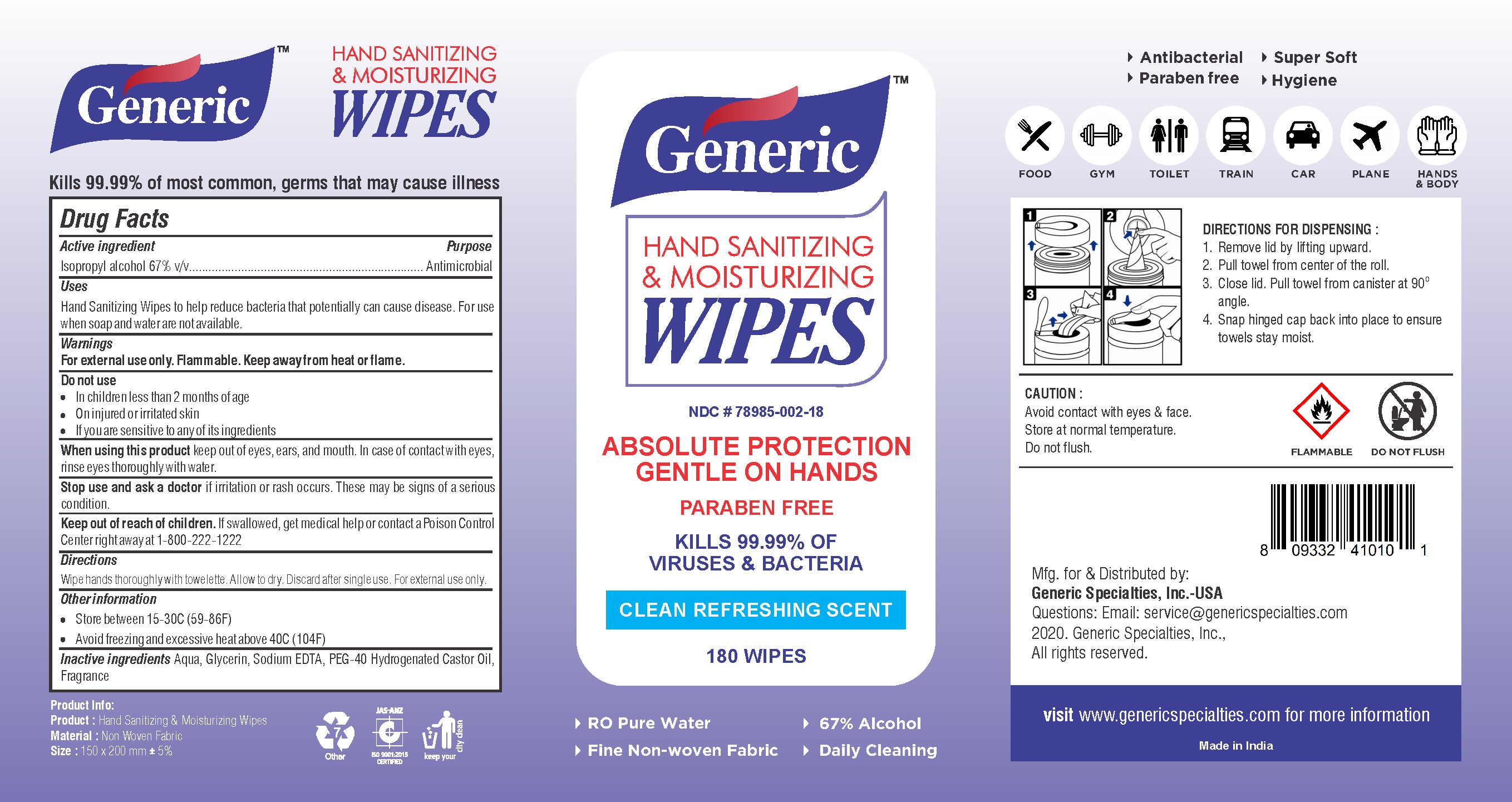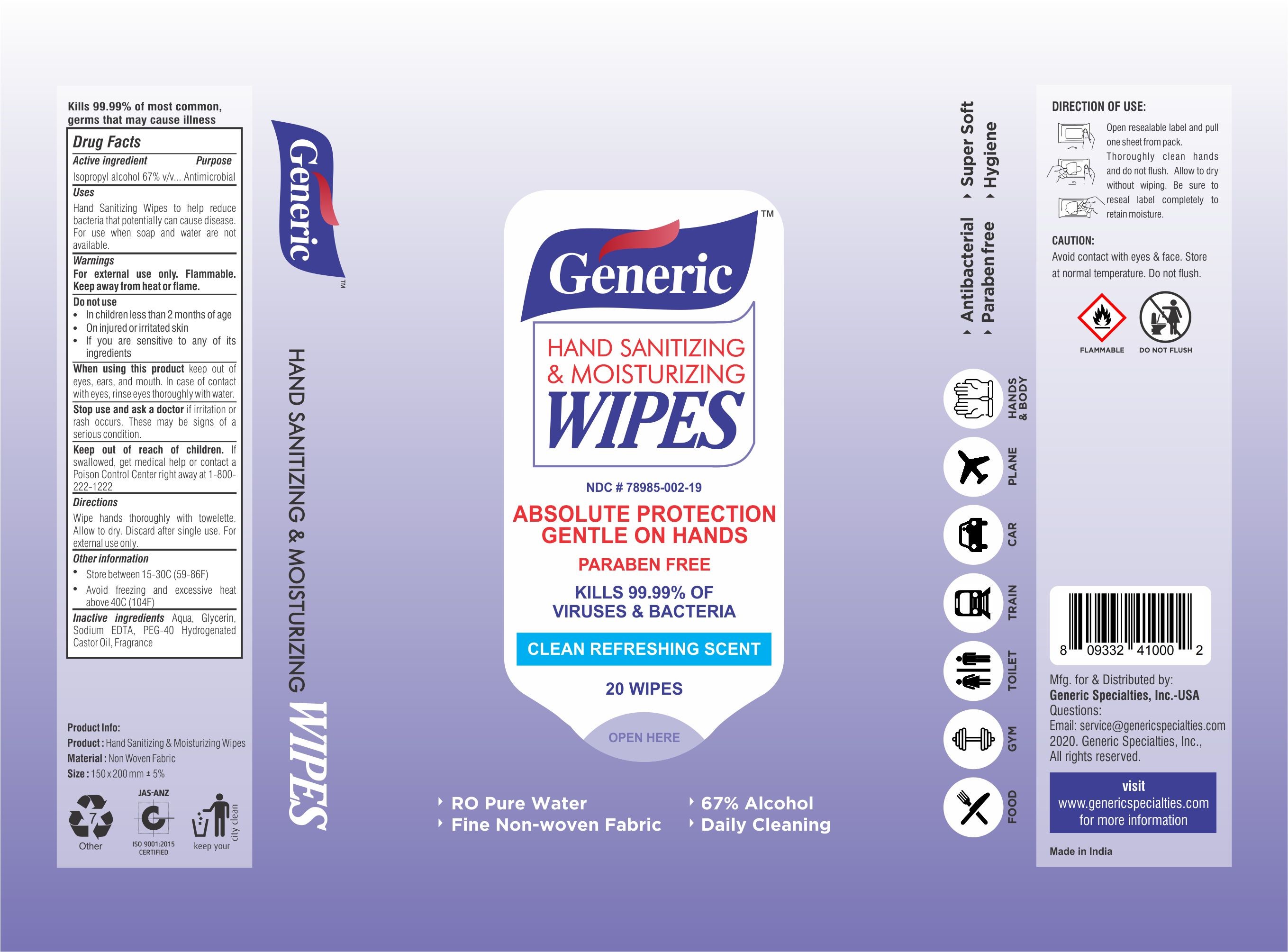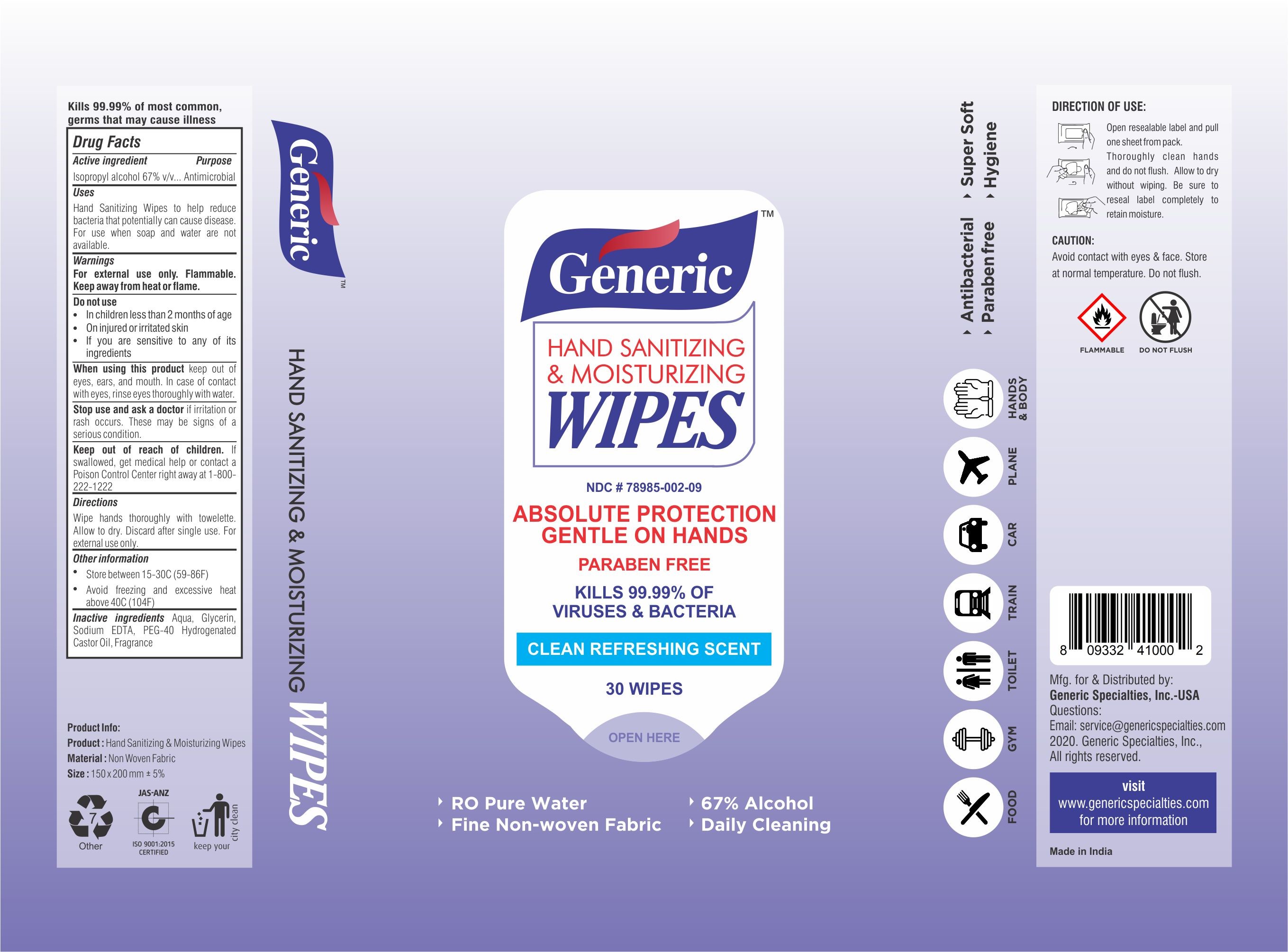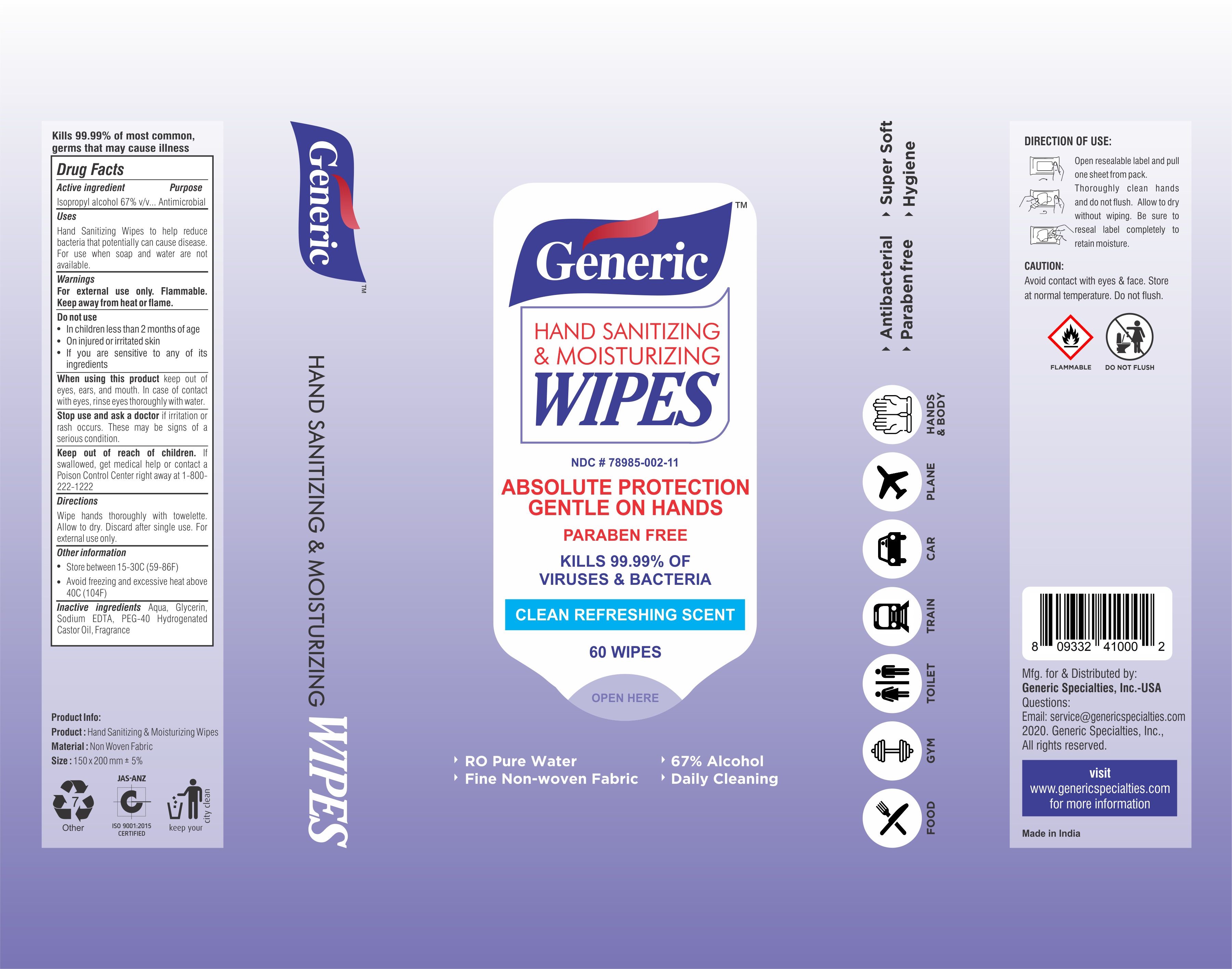 DRUG LABEL: Hand Sanitizing and Moisturizing Wipes
NDC: 78985-002 | Form: SWAB
Manufacturer: Generic Specialties, Inc.
Category: otc | Type: HUMAN OTC DRUG LABEL
Date: 20200917

ACTIVE INGREDIENTS: ISOPROPYL ALCOHOL 67 mL/100 1
INACTIVE INGREDIENTS: WATER; EDETATE SODIUM 0.15 mL/100 1; GLYCERIN 0.5 mL/100 1; POLYOXYL 40 HYDROGENATED CASTOR OIL 0.2 mL/100 1

This is a hand sanitizing & moisturizing wipes manufactured according to the Temporary Policy for Preparation of Certain Alcohol-Based Hand Sanitizer Products During the Public Health Emergency (CoViD-19); Guidance for Industry.

The hand sanitizing & moisturizing wipes are manufactured using only the following United States Pharmacopoeia (USP) grade ingredients in the preparation of the product (percentage in final product formulation) consistent with World Health Organization (WHO) recommendations:

Alcohol (Isopropyl alcohol) (USP or Food Chemical Codex (FCC) grade) (67%, volume/volume (v/v)) in an aqueous solution denatured according to Alcohol and Tobacco Tax and Trade Bureau regulations in 27 CFR part 20.
Glycerin

Sodium EDTA

PEG 40 Hydrogenated Castor Oil

Fragrance
Aqua.

The firm does not add other active or inactive ingredients. Different or additional ingredients may impact the quality and potency of the product

Active Ingredient(s)

Isopropyl Alcohol 67% v/v. Purpose: Antimicrobial, Antibacterial

Purpose

Antimicrobial, Antibacterial Hand sanitizing and moisturizing wipes

Use

Hand Sanitizing wipes to help reduce bacteria that potentially can cause disease. For use when soap and water are not available.

Warnings

For external use only. Flammable. Keep away from heat or flame

Do not use

- in children less than 2 months of age
- on injured or irritated skin
- If you are sensitive to any of its ingredients

When using this product keep out of eyes, ears, and mouth. In case of contact with eyes, rinse eyes thoroughly with water.
Stop use and ask a doctor if irritation or rash occurs. These may be signs of a serious condition.
Keep out of reach of children. If swallowed, get medical help or contact a Poison Control Center right away at 1-800-222-1222

Stop use and ask a doctor if irritation or rash occurs. These may be signs of a serious condition.

Keep out of reach of children. If swallowed, get medical help or contact a Poison Control Center right away at 1-800-222-1222

Directions

- Wipe hands thoroughly with a towelette. Allow to dry. Discard after a single-use. For External use only.

Other information

- Store between 15-30C (59-86F)
- Avoid freezing and excessive heat above 40C (104F)

Inactive ingredients

Aqua, Glycerin, Sodium EDTA, PEG 40 Hydrogenated Castor Oil, Fragrance

RECENT MAJOR CHANGES

Hand sanitizing wipes to help reduce bacteria that potentially can cause disease. for use when soap and water are not available.

Wipe hands thoroughly with a towelette. Allow to dry. Discard after a single-use. For External use only.